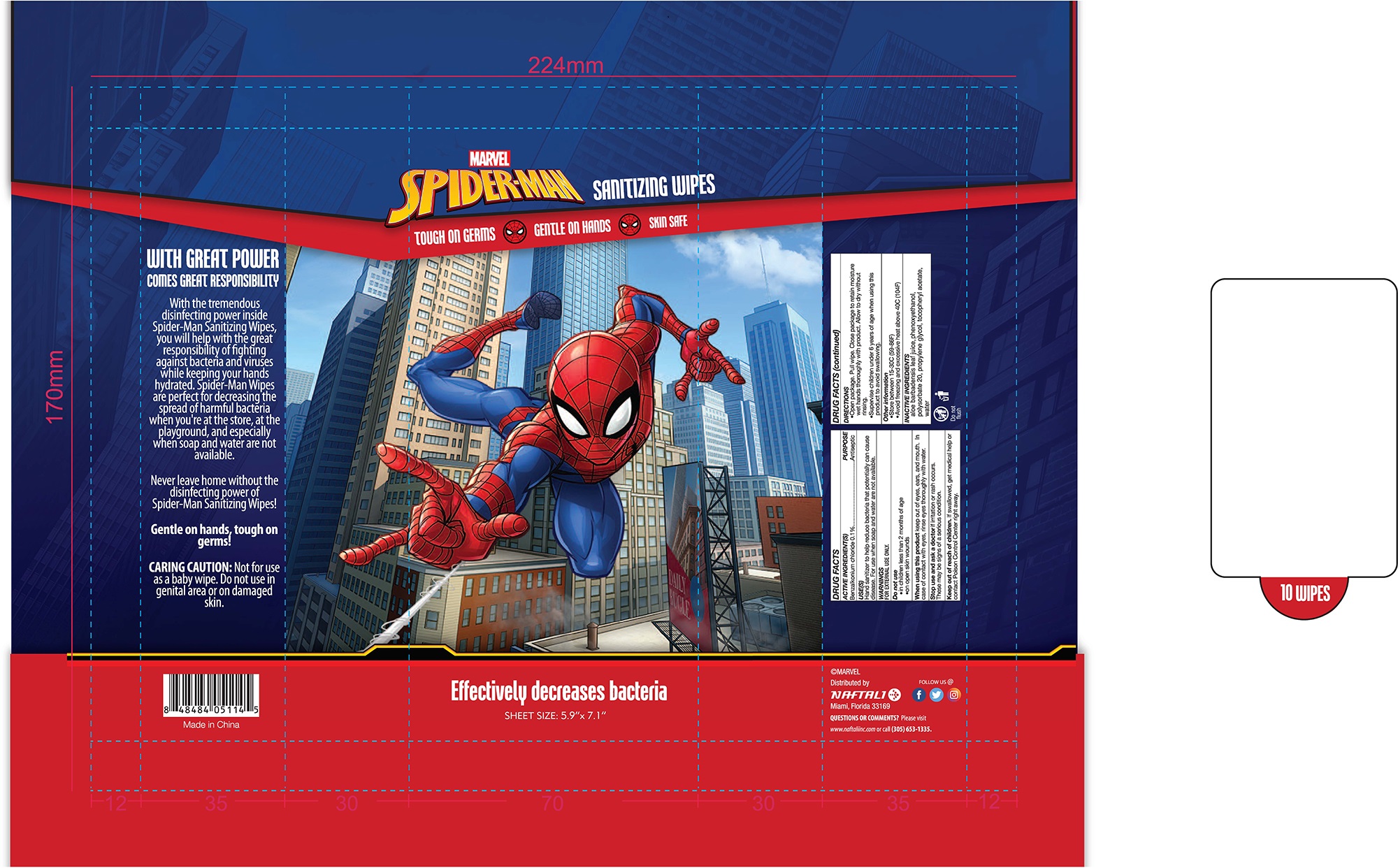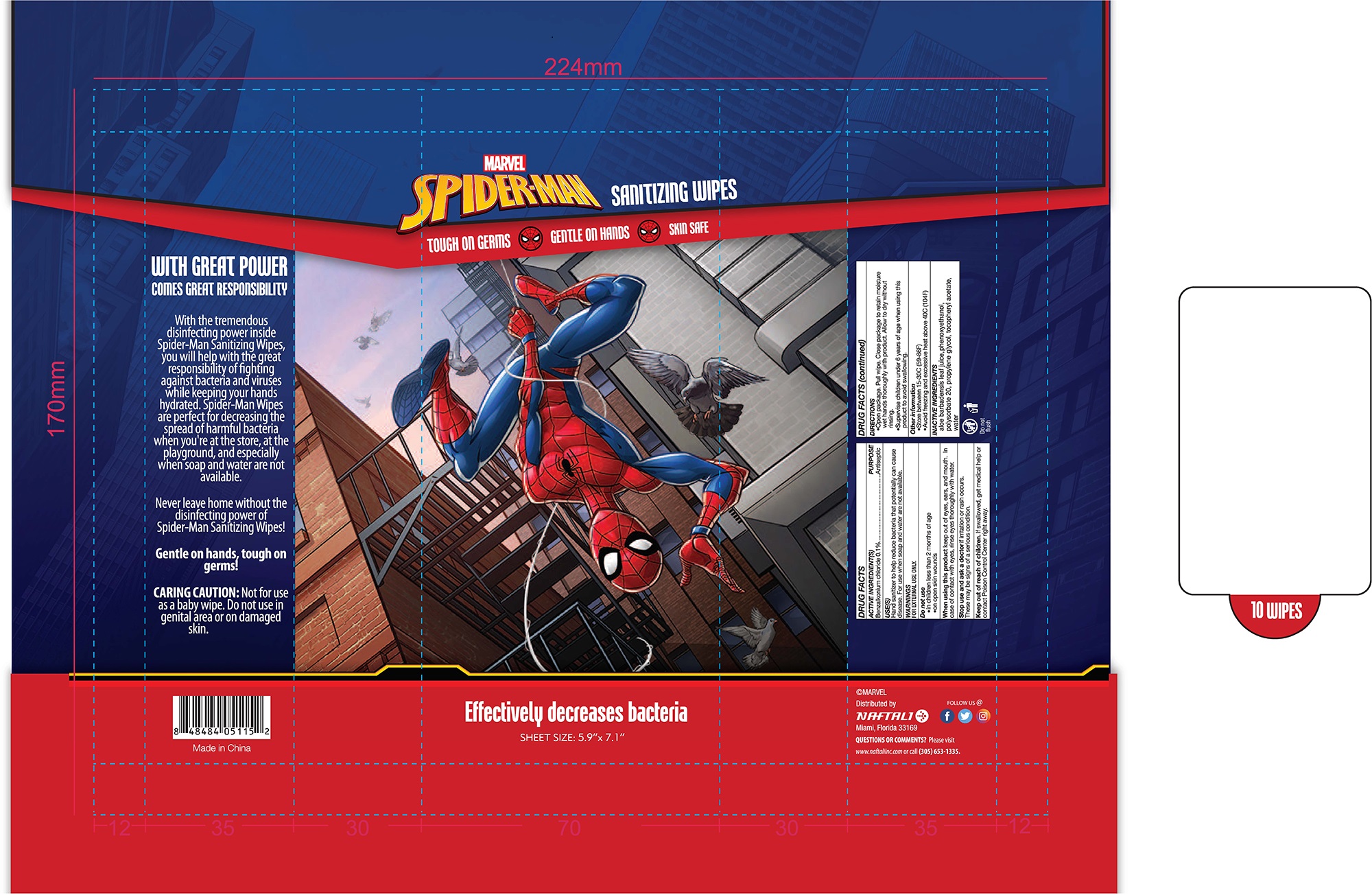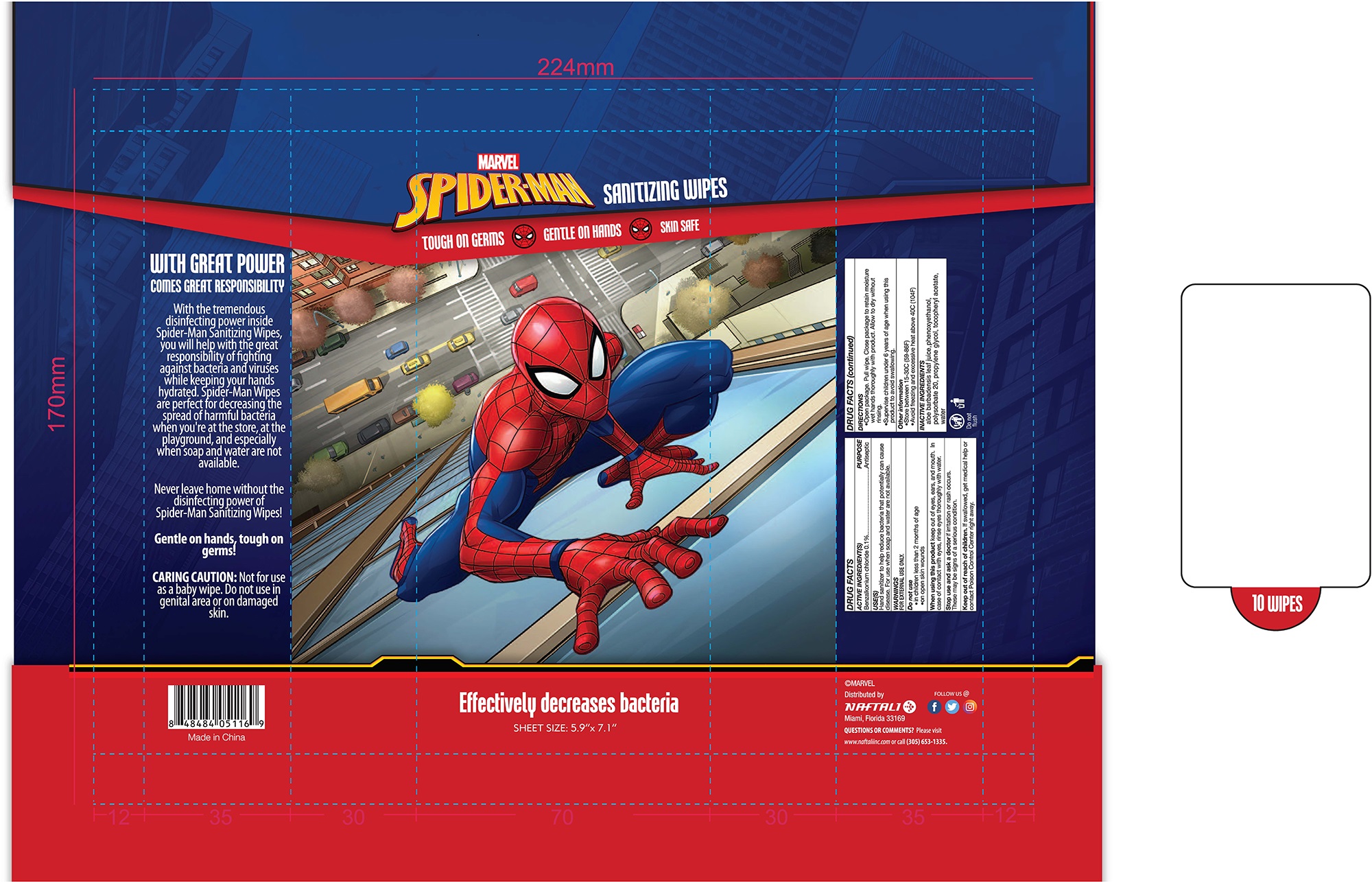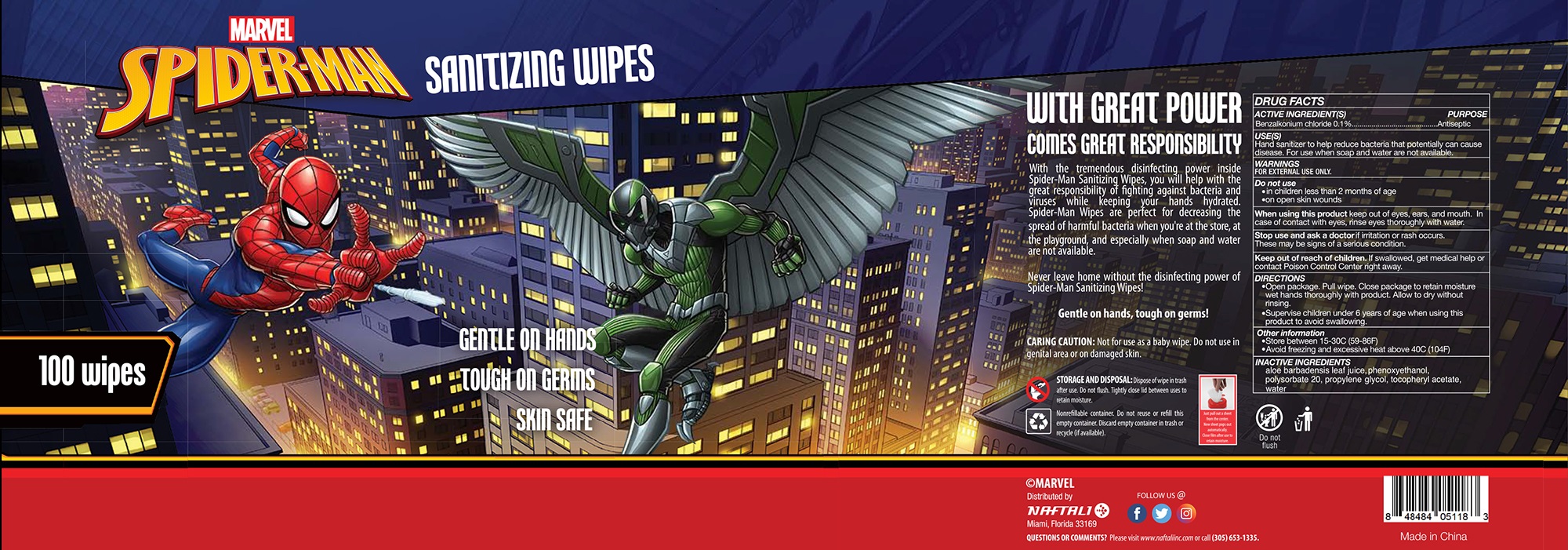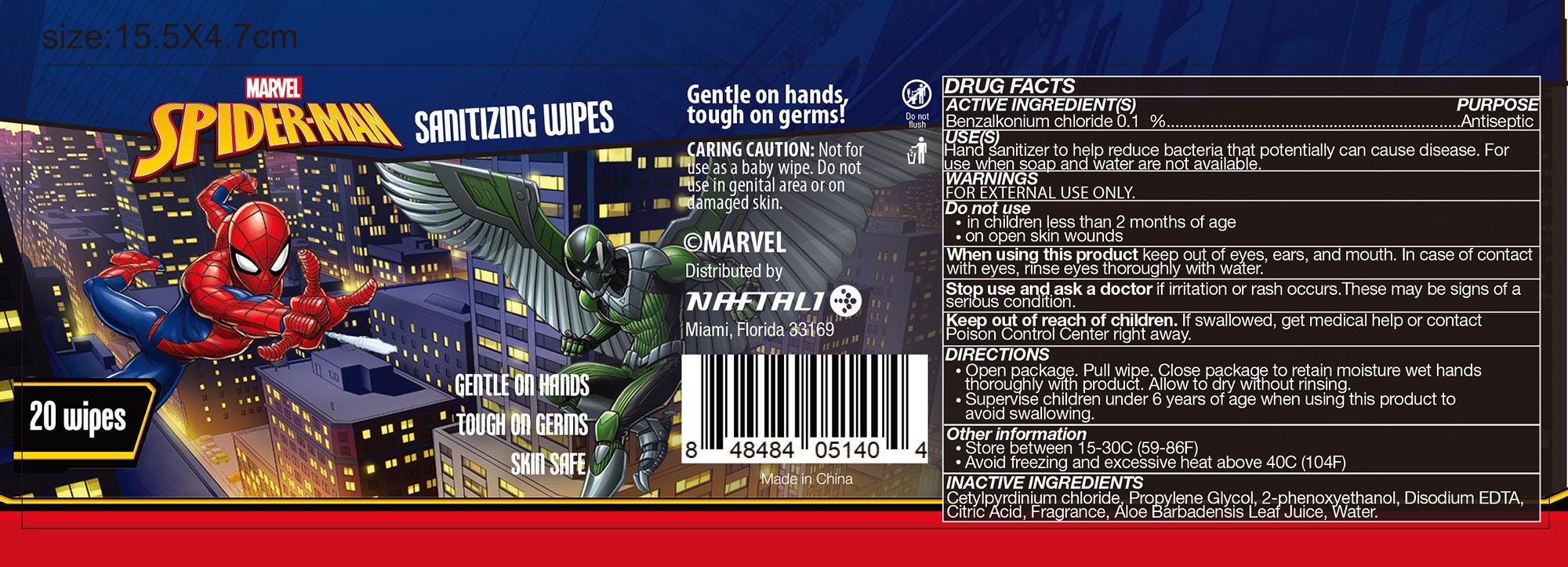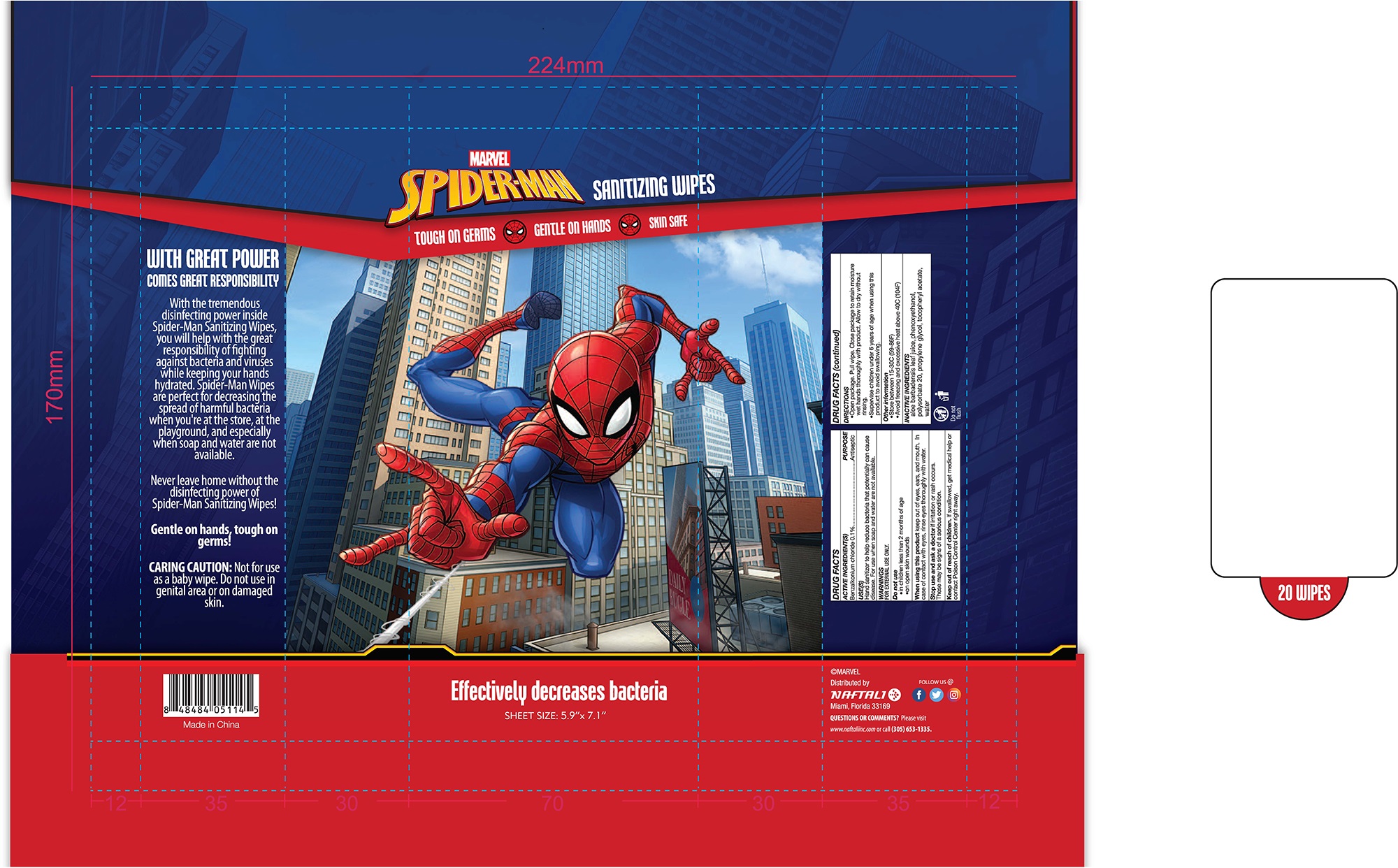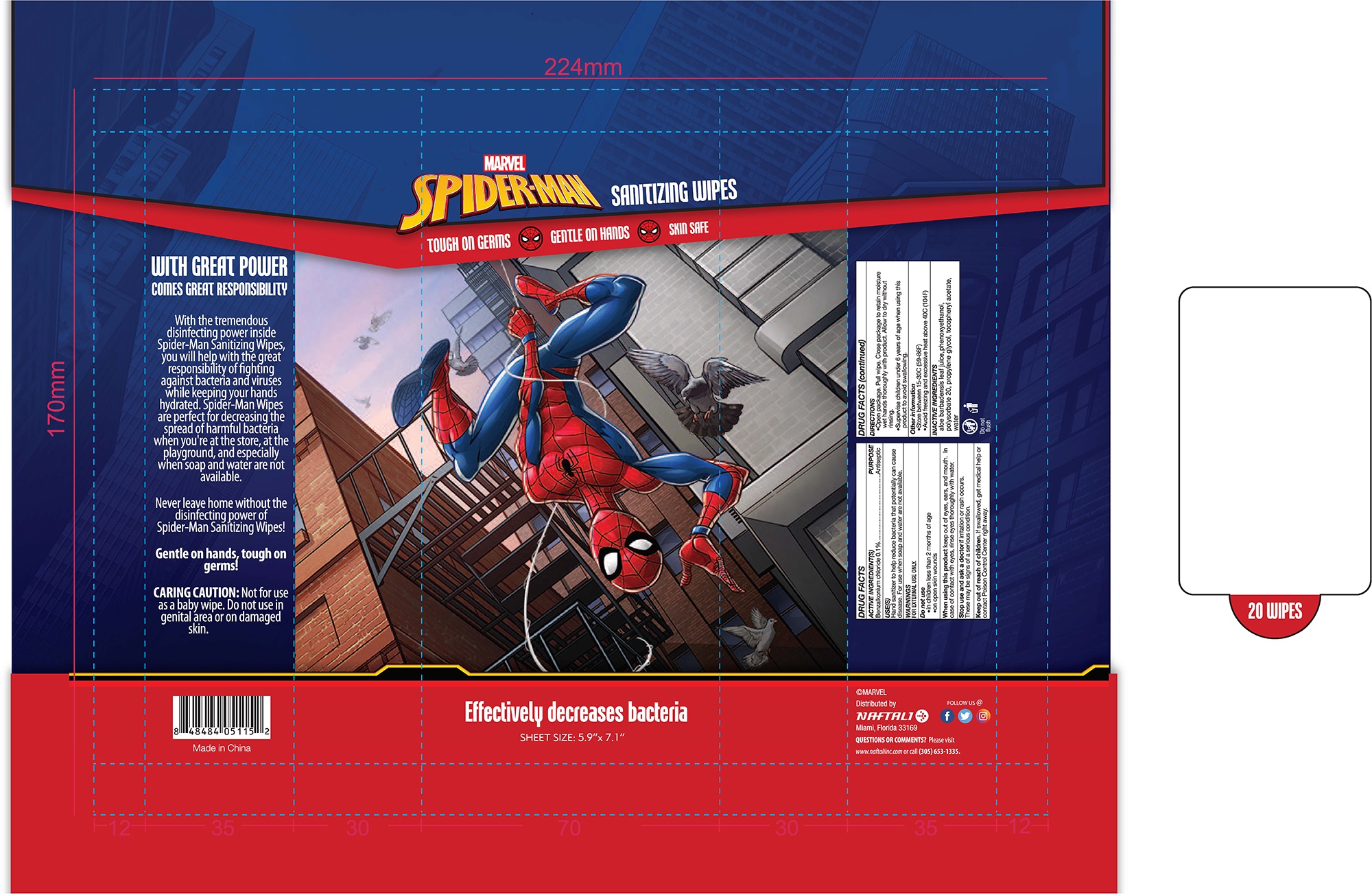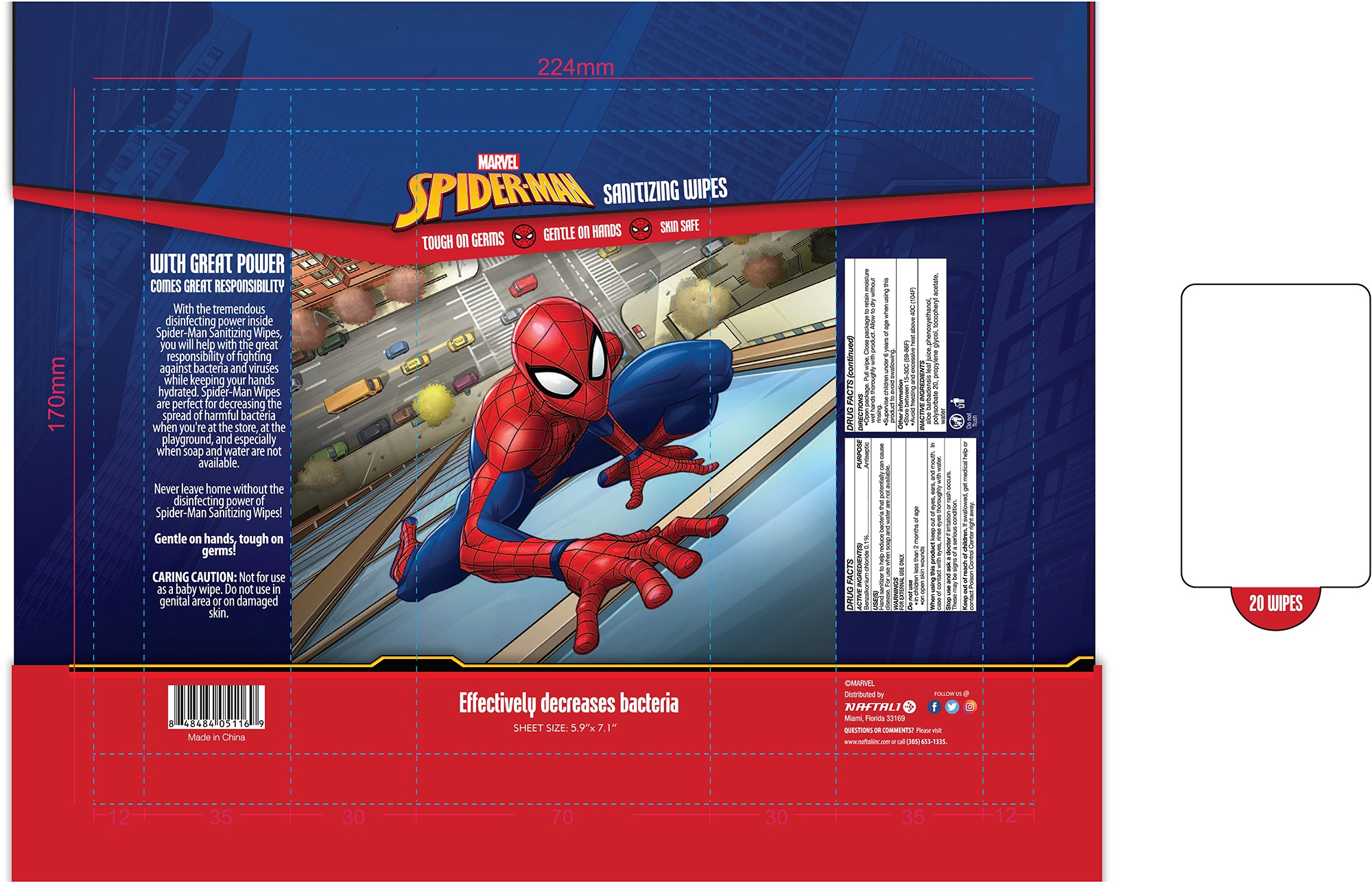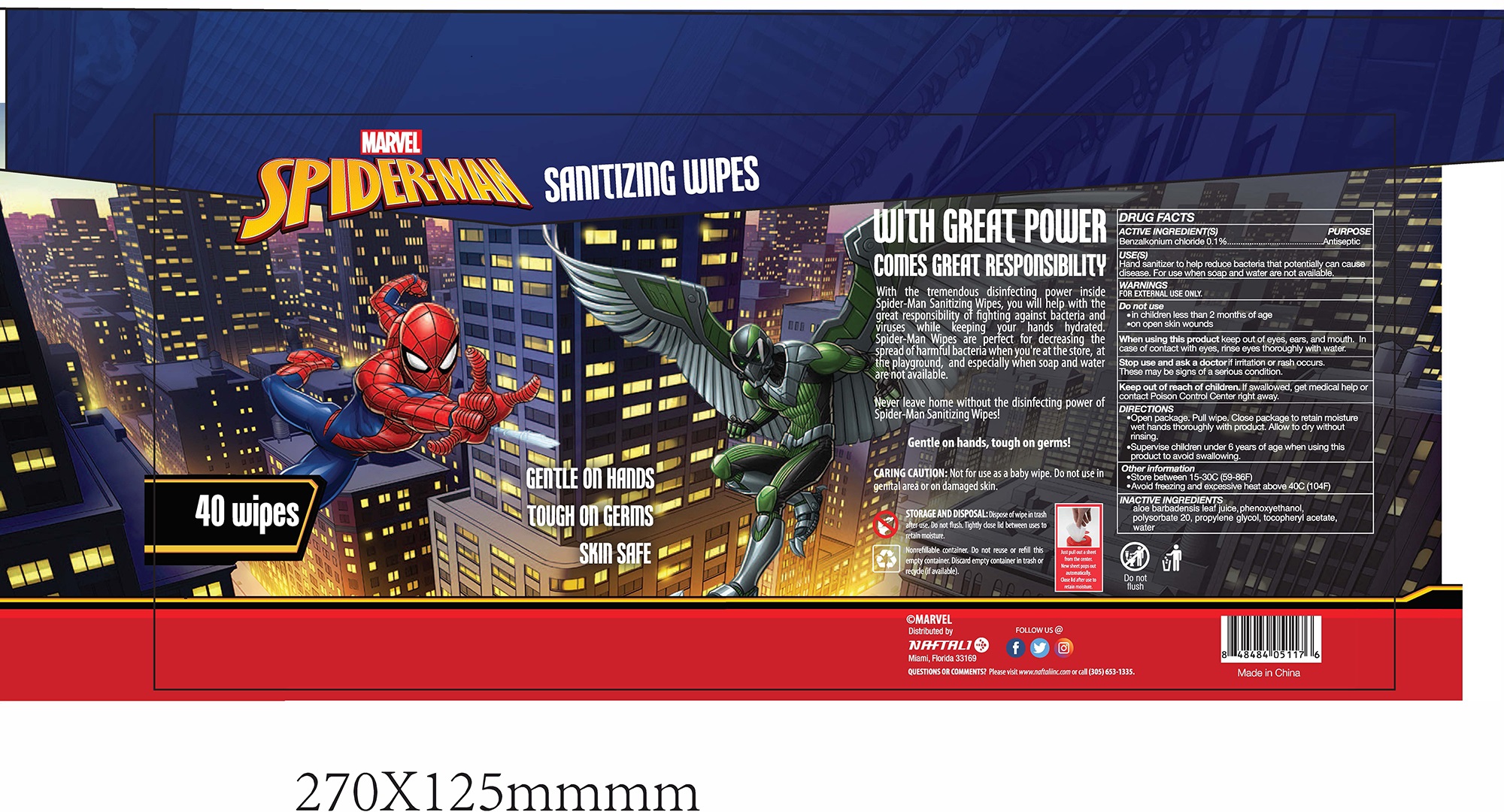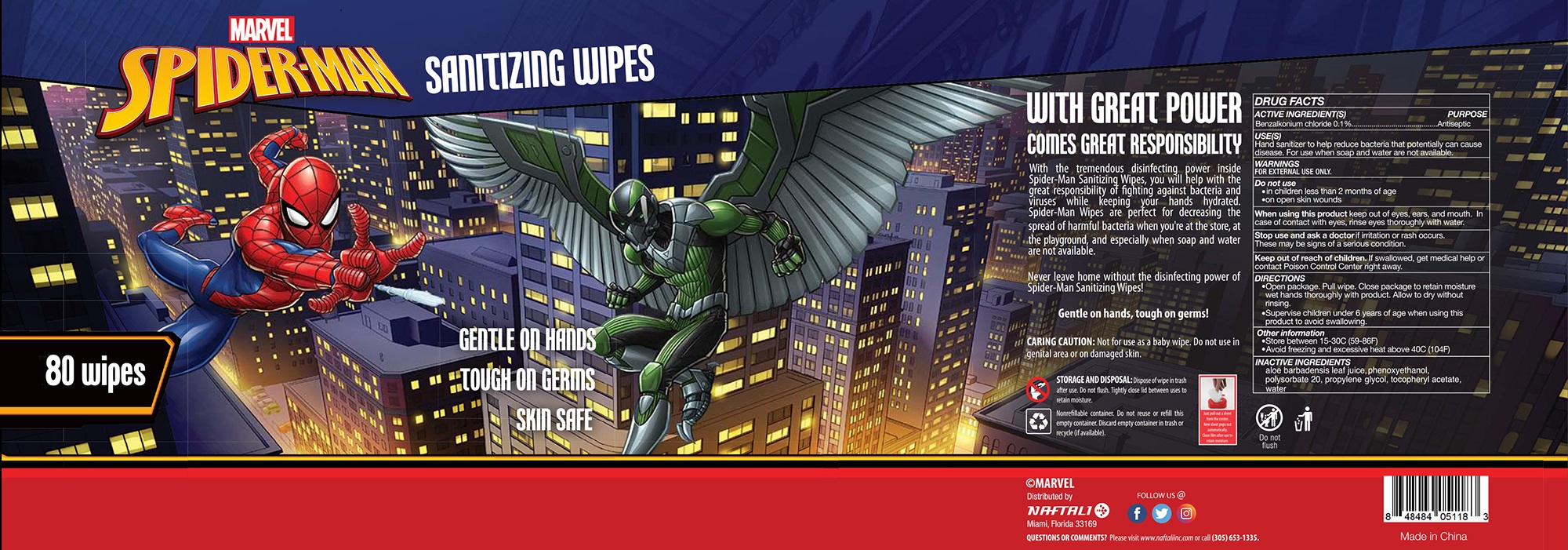 DRUG LABEL: ANTIBACTERIAL WIPES UNSCENTED
NDC: 80593-007 | Form: SOLUTION
Manufacturer: ZHANGZHOU WANSIKE ELECTRONICS CO., LTD
Category: otc | Type: HUMAN OTC DRUG LABEL
Date: 20210222

ACTIVE INGREDIENTS: BENZALKONIUM CHLORIDE 0.1 g/100 1
INACTIVE INGREDIENTS: PROPYLENE GLYCOL; ALOE VERA LEAF; POLYSORBATE 20; PHENOXYETHANOL; .ALPHA.-TOCOPHEROL ACETATE; WATER

80593-007
ANTIBACTERIAL WIPES UNSCENTED

Active Ingredient(s)

Benzalkonium Chloride 0.1%

Purpose

Antiseptic

Use

Hand sanitizer to help reduce bacteria that potentially can cause disease.For use when soap and water are not available.

Warnings

FOR EXTERNAL USE ONLY.

Do not use
·in children less than 2 months of age
·on open skin wounds

When using this product keep out of eyes, ears, and mouth.In case of contact with eyes, rinse eyes thoroughly with water.

Stop use and ask a doctor if irritation or rash occurs. These maybe signs of a serious condition.

Keep out of reach of children.If swallowed, get medical help or contact Poison Control Center right away.

Do not use

·in children less than 2 months of age
·on open skin wounds

When using this product keep out of eyes, ears, and mouth.In case of contact with eyes, rinse eyes thoroughly with water.

Stop use and ask a doctor if irritation or rash occurs. These maybe signs of a serious condition.

Keep out of reach of children.If swallowed, get medical help or contact Poison Control Center right away.

Stop use and ask a doctor if irritation or rash occurs. These maybe signs of a serious condition.

Keep out of reach of children. If swallowed, get medical help or contact Poison Control Center right away.

Directions

·Open package.Pull wipe.Close package to retain moisture wet hands thoroughly with product.Allow to dry without rinsing.
·Supervise children under 6 years of age when using this product to avoid swallowing.

Other information

Store between 15-30C (59-86F)
Avoid freezing and exessive heat aboce 40C (104F)

Inactive ingredients

Aloe Barbadensis Leaf Juice, Phenoxyethanol, Polysorbate 20, Propylene Glycol, Tocopheryl Acetate, Water

Package Label - Principal Display Panel

10 solution in 1 package 80593-007-01

10 solution in 1 package 80593-007-02

10 solution in 1 package 80593-007-03

20 solution in 1 package 80593-007-04

20 solution in 1 package 80593-007-05

20 solution in 1 package 80593-007-06

20 solution in 1 canister 80593-007-07

40 solution in 1 canister 80593-007-08

80 solution in 1 canister 80593-007-09

100 solution in 1 canister 80593-007-10